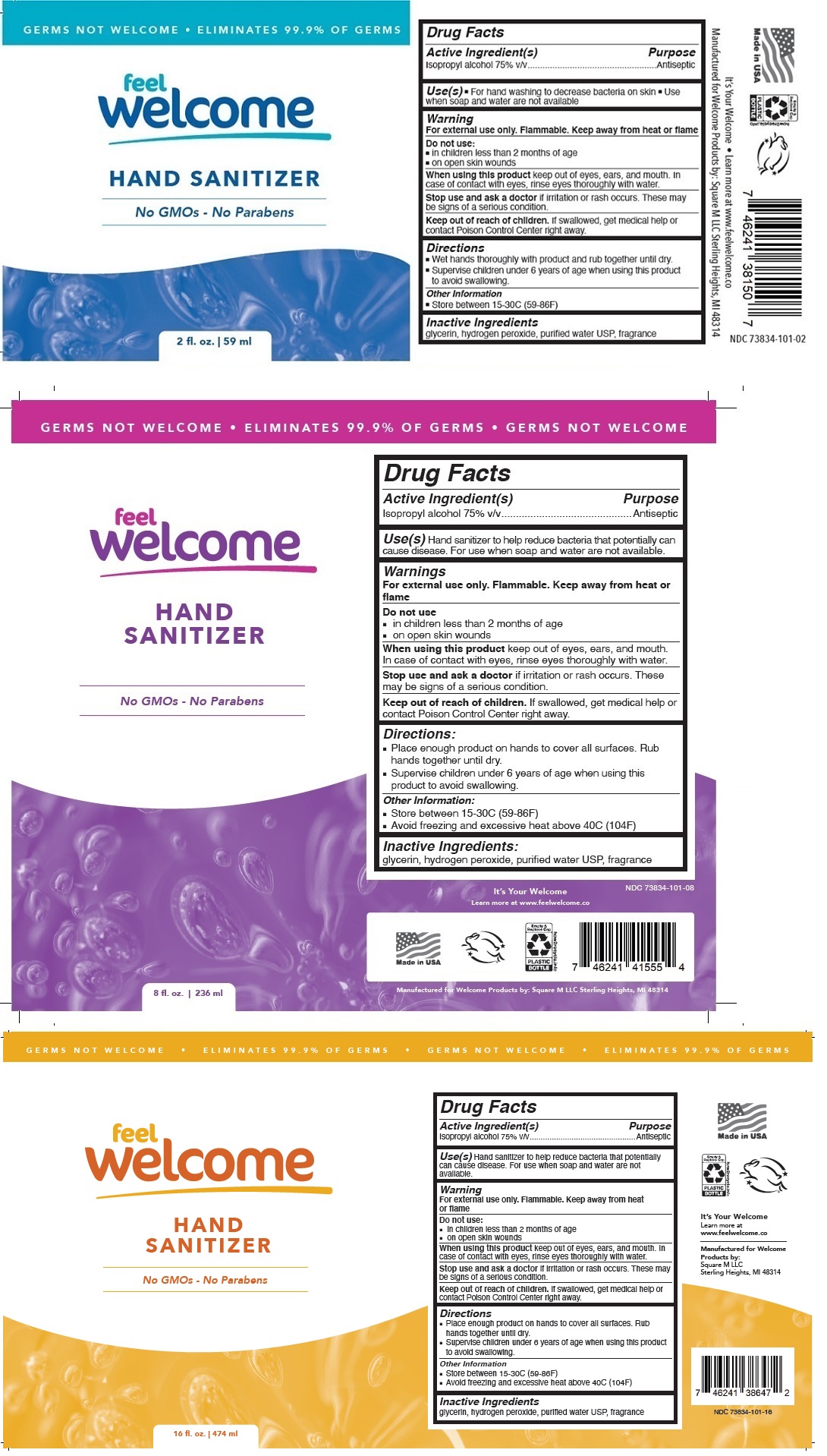 DRUG LABEL: FEEL WELCOME HAND SANITIZER
NDC: 73834-101 | Form: LIQUID
Manufacturer: Square M Llc
Category: otc | Type: HUMAN OTC DRUG LABEL
Date: 20201201

ACTIVE INGREDIENTS: ISOPROPYL ALCOHOL 75 mL/100 mL
INACTIVE INGREDIENTS: GLYCERIN; HYDROGEN PEROXIDE; WATER

feel welcome HAND SANITIZER

Active Ingredient(s)

Isopropyl alcohol 75% v/v

Purpose

Antiseptic

INDICATIONS AND USAGE

Use(s) Hand sanitizer to help reduce bacteria that potentially can cause disease. For use when soap and water are not available.

Warning

For external use only. Flammable. Keep away from heat or flame
Do not use:

■ in children less than 2 months of age

■ on open skin wounds

When using this product keep out of eyes, ears, and mouth. In case of contact with eyes, rinse eyes thoroughly with water.
Stop use and ask a doctor if irritation or rash occurs. These may be signs of a serious condition.

Keep out of reach of children. If swallowed, get medical help or contact Poison Control Center right away.

Directions

■ Place enough product on hands to cover all surfaces. Rub hands together until dry.
■ Supervise children under 6 years of age when using this product to avoid swallowing.

Other Information

■ Store between 15-30°C (59-86°F)

■ Avoid freezing and excessive heat above 40°C (104°F)

Inactive Ingredients

glycerin, hydrogen peroxide, purified water USP, fragrance

GERMS NOT WELCOME • ELIMINATES 99.9% OF GERMS

No GMOs - No Parabens

It’s Your Welcome • Learn more at www.feelwelcome.co

Manufactured for Welcome Products by: Square M LLC Sterling Heights, MI 48314

Made in USA